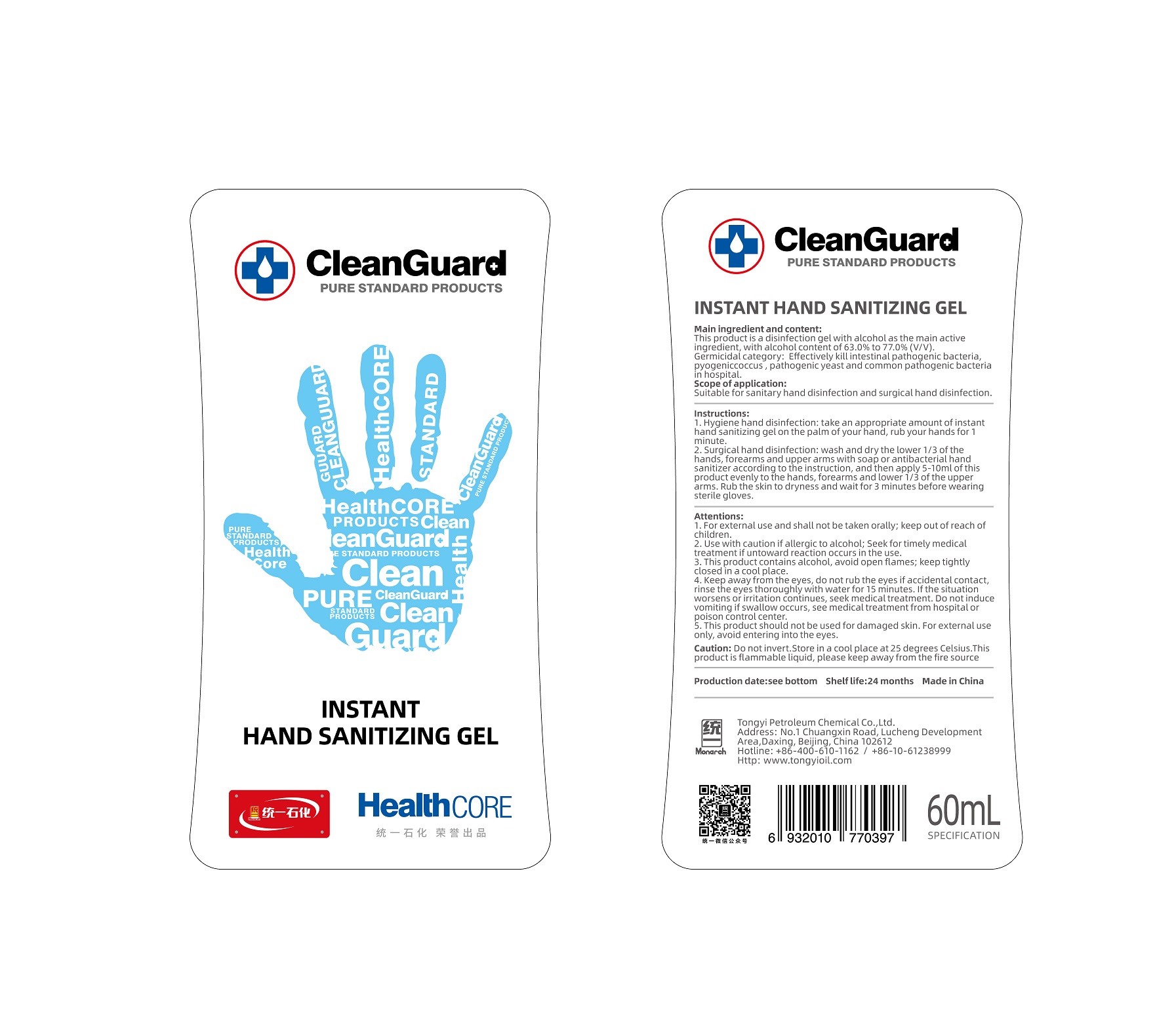 DRUG LABEL: TongYi CleanGuard Hand Sanitizer
NDC: 73681-6061 | Form: GEL
Manufacturer: Tongyi Petroleum Chemical Co., Ltd.
Category: otc | Type: HUMAN OTC DRUG LABEL
Date: 20200401

ACTIVE INGREDIENTS: ALCOHOL 42 mL/60 mL
INACTIVE INGREDIENTS: 1,3-BUTYLENEGLYCOL DIMETHACRYLATE 5 mL/60 mL; WATER 15 mL/60 mL

TongYi, Hand Sanitizer Gel, 60mL *96

Active ingredient

Ethanol

Inactive ingredient

Water

Acrylate

Purpose

Effectively kill intestinal pathogenic bacteria, pyogenic coccus, pathogenic yeast and common pathogenic bacteria in hospital.

When using

Effectively kill intestinal pathogenic bacteria, pyogenic coccus, pathogenic yeast and common pathogenic bacteria in hospital.

Do not use

Use only as directed.
Do not use for cases not directed.

Stop use

Stop use if the product's volatile gases cause discomfort, or if you experience respiratory irritation such as cough, asthma, or difficulty breathing.

Ask doctor

If using the product causes serious discomfort, ask or see your doctor.

Ask doctor/pharmacist

If using the product causes serious discomfort, ask or see your doctor/pharmacist.

Keep out of reach of children

Questions

Please contact with us at the phone number +86-10-61238999 when you have any questions.

Pregnancy or breast feeding

Pregnant or breast feeding women shall follow doctor advice.

Indications & usage

1. Hygiene hand disinfection: take an appropriate amount of instant hand sanitizing gel on the palm of your hand, rub your hands for 1 minute.

2. Surgical hand disinfection: wash and dry the lower 1/3 of the hands, forearms and upper arms with soap or antibacterial hand sanitizer according to the instruction, and then apply 5-10ml of this product evenly to the hands, forearms and lower 1/3 of the upper arms. Rub the skin to dryness and wait for 3 minutes before wearing sterile gloves.

Dosage & administration

Use it as needed, after following the usage instructions.

For external use only.

Dosage forms & strengths

This product is gel dosage form.
The active ingredient strength is 70%.

Warnings

1. For external use and shall not be taken orally; keep out of reach of children.

2. Use with caution if allergic to alcohol; Seek for timely medical treatment if untoward reaction occurs in the use.

3. This product contains alcohol, avoid open flames; keep tightly closed in a cool place.

4. Keep away from the eyes, do not rub the eyes if accidental contact, rinse the eyes thoroughly with water for 15 minutes. If the situation worsens or irritation continues, seek medical treatment. Do not induce vomiting if swallow occurs, see medical treatment from hospital or poison control center.

5. This product should not be used for damaged skin. For external use only, avoid entering into the eyes.